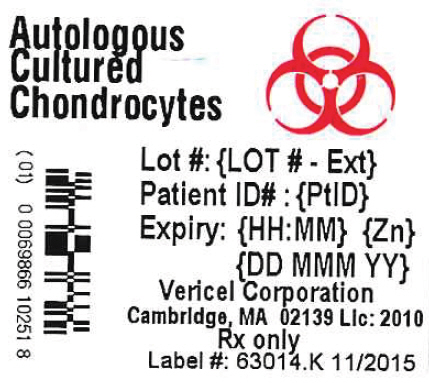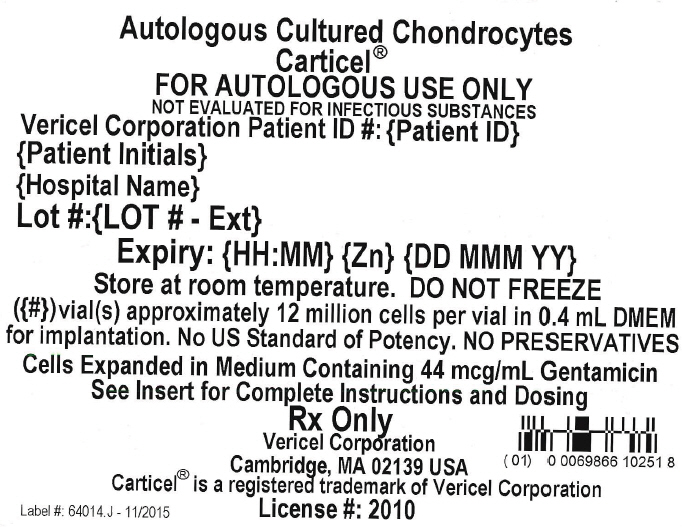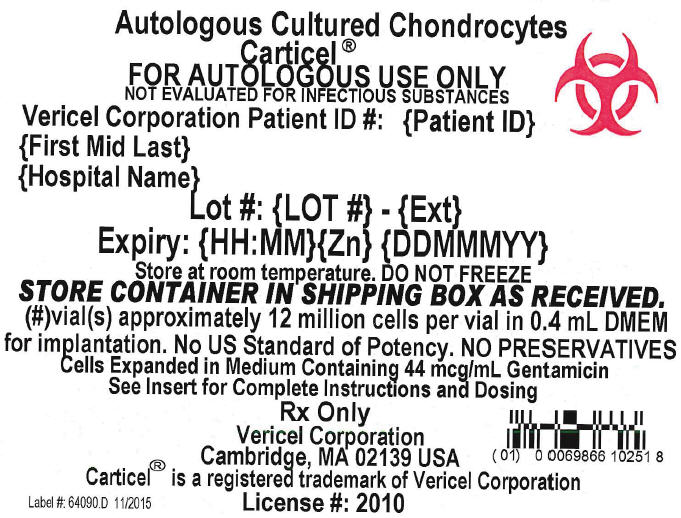 DRUG LABEL: CARTICEL
NDC: 69866-1025 | Form: IMPLANT
Manufacturer: Vericel Corporation
Category: prescription | Type: HUMAN PRESCRIPTION DRUG LABEL
Date: 20170206

ACTIVE INGREDIENTS: autologous cultured chondrocytes 1.2e+007 1/1 1

HIGHLIGHTS OF PRESCRIBING INFORMATION

These highlights do not include all the information needed to use Carticel® safely and effectively. See full prescribing information for Carticel.
Carticel (autologous cultured chondrocytes)
For Autologous Implantation
Initial U.S. Approval: 1997

1. INDICATIONS AND USAGE

Carticel is an autologous cellular product indicated for the repair of symptomatic cartilage defects of the femoral condyle (medial, lateral or trochlea), caused by acute or repetitive trauma, in patients who have had an inadequate response to a prior arthroscopic or other surgical repair procedure (e.g., debridement, microfracture, drilling/abrasion arthroplasty, or osteochondral allograft/autograft). (1)

Carticel should be used only in conjunction with debridement, placement of a periosteal flap and rehabilitation. (1)

Carticel is not indicated for:

- treatment of cartilage damage associated with generalized osteoarthritis. (1)
- patients with total meniscectomy unless surgically reconstructed prior to or concurrent with Carticel implantation. (1)

2. DOSAGE AND ADMINISTRATION

For Autologous Implantation Only

- Carticel should be administered only by physicians who have completed Vericel's Surgeon Training Program. (2.3)
- Implantation of the Carticel product is performed during arthrotomy and requires both preparation of the defect bed and a periosteal flap to secure the implant.
- See the Carticel Surgical Manual, Vericel document #65021 for instructions on the performance of these procedures. (2.3)

3. DOSAGE FORMS AND STRENGTHS

Each Carticel® vial of autologous cultured chondrocytes contains approximately 12 million cells per vial. (3)

4. CONTRAINDICATIONS

Do not use in patients with a known history of hypersensitivity to gentamicin, other aminoglycosides or materials of bovine origin. (4)

5. WARNINGS AND PRECAUTIONS

- The necessity of subsequent surgical procedures, primarily arthroscopic, following Carticel implantation is common. In the STAR study, 49% of patients underwent a subsequent surgical procedure, irrespective of relationship to Carticel. (5.1, 6.2)
- Carticel is not routinely tested for transmissible infectious diseases and may transmit diseases to the health care provider handling the product. Carticel is intended for autologous use only. (5.2)
- Pre-existing conditions, including meniscal tears, joint instability, or malalignment should be assessed and treated prior to or concurrent with Carticel implantation. (5.3)
- Carticel should not be used in patients who have previously had cancer in the bones, cartilage, fat or muscle of the treated limb. (5.4)

6. ADVERSE REACTIONS

The most common serious adverse events (> 5% of patients), derived from the STAR study include arthrofibrosis/joint adhesions, graft overgrowth, chondromalacia or chondrosis, cartilage injury, graft complication, meniscal lesion and graft delamination. (6.2)

To report SUSPECTED ADVERSE REACTIONS, contact Vericel at 1-800-453-6948 or contact FDA at 1-800-FDA-1088 or www.fda.gov/medwatch

8. USE IN SPECIFIC POPULATIONS

Use in children or patients over age 65 has not been assessed. (8)

FULL PRESCRIBING INFORMATION

1. INDICATIONS AND USAGE

Carticel® is indicated for the repair of symptomatic cartilage defects of the femoral condyle (medial, lateral or trochlea), caused by acute or repetitive trauma, in patients who have had an inadequate response to a prior arthroscopic or other surgical repair procedure (e.g., debridement, microfracture, drilling/abrasion arthroplasty, or osteochondral allograft/autograft).

Carticel should be used only in conjunction with debridement, placement of a periosteal flap and rehabilitation. The independent contributions of the autologous cultured chondrocytes and other components of the therapy to outcome are unknown.

Carticel is not indicated for the treatment of cartilage damage associated with generalized osteoarthritis.

Carticel is not recommended for patients with total meniscectomy unless surgically reconstructed prior to or concurrent with Carticel implantation.

2. DOSAGE AND ADMINISTRATION

For Autologous Implantation Only

2.1 Dosage

Patients in the Swedish series [see Clinical Studies (14)] received a wide range of cell doses per cm^2 of defect. Available data on 70 of 78 patients with femoral condyle defects showed a median dose of 1.6 million cells/cm^2 of defect. The middle 80% of these patients received from 0.64 million to 3.3 million cells/cm^2.

Each Carticel finished product vial contains approximately 12 million cells. Vericel provides a single vial for each defect measuring ≤ 7 cm^2. Two vials of Carticel are provided for defects 7 to 14 cm^2, and three vials are provided for defects > 14 cm^2. This is based on Vericel's greater than 10 years of experience with Carticel.

2.2 Handling Precautions and Preparation

2.2.1 Handling Precautions

The Carticel product is intended solely for autologous use. Prior to Carticel implantation, match the patient name and ID number on the certificate of analysis to the patient's chart and the patient ID on the shipping box, transport cylinder and vial.

Health care providers should employ universal precautions in handling the biopsy samples and the Carticel product [see Risk of Transmissible Infectious Diseases (5.2)].

Refer to the Indications and Usage (1) and Warnings and Precautions (5) Sections for additional considerations regarding the use of Carticel.

2.2.2 Preparation

NOTE:

The exterior of the Carticel vial containing the cultured cells is NOT sterile. Follow strict sterile technique protocols.

When treating a defect that requires multiple vials of cells, resuspend, aspirate and inject one vial at a time.

1. Remove red plastic lid from vial. Wipe the vial surface and lid with alcohol.
2. Inspect vial contents for particulates, discoloration or turbidity. The cellular product appears as a yellowish clump in the bottom of the vial. Do not administer if contents appear turbid prior to cell suspension.
3. While holding vial in a vertical position, insert the needle of the intraspinal catheter into the vial. The needle must be positioned just above the fluid level. Slowly remove the inner needle from the catheter, leaving flexible tip behind. Attach a tuberculin syringe to catheter.
4. Lower the catheter tip into the media and position just above the cell pellet. Aspirate all the medium from the vial leaving only the cell pellet behind. Slowly expel medium back into the vial. This action will break the cell pellet and resuspend the cells in the medium.
5. Lower the catheter tip to the base of the vial and aspirate all contents into syringe, leaving the vial empty. Slowly inject the contents into the vial again. This will assure complete suspension of the cells. Repeat these steps as needed to ensure all cells are resuspended. Cell resuspension is complete when cell particles are no longer apparent, and the medium is a consistent, "cloudy" mixture. Aspirate all contents of vial into syringe. Always hold syringe vertical to keep an air pocket at the proximal end of syringe.

2.3 Administration

Implantation of the Carticel product should be restricted to physicians who have completed Vericel's Surgeon Training Program.

Implantation of the Carticel® product is performed during arthrotomy and requires both preparation of the defect bed and a periosteal flap to secure the implant. Complete hemostasis must be achieved prior to periosteal fixation and cell implantation. See the Carticel Surgical Manual, Vericel document #65021 for instructions on the performance of these procedures.

2.3.1 Implantation

1. Insert the catheter tip through the superior opening of the periosteal chamber at the site of the defect. Advance catheter to most inferior aspect of the defect.
2. Slowly inject a cell dose while moving the catheter tip from side to side and withdrawing the catheter proximally. This will ensure an even distribution of the cells throughout the defect.
3. Complete the implantation by closing the superior opening of the periosteum as instructed. See Carticel Surgical Manual, Vericel document #65021.

3. DOSAGE FORMS AND STRENGTHS

One vial of Carticel (autologous cultured chondrocytes) contains approximately 12 million cells.

4. CONTRAINDICATIONS

Carticel should not be used in patients with a known history of hypersensitivity to gentamicin, other aminoglycosides or materials of bovine origin.

Gentamicin is added to both the cartilage biopsy transport media and in the culture media used during the processing of Carticel. Residual quantities of gentamicin up to 5 µg/mL are present in the Carticel product.

Fetal bovine serum is a component in the culture medium used to propagate the autologous chondrocytes. Trace quantities of bovine-derived proteins may be present in the Carticel product.

5. WARNINGS AND PRECAUTIONS

5.1 Subsequent Surgical Procedures

Review of the data from the Study of the Treatment of Articular Repair (STAR) and the Registry Based Study (RBS) [see Clinical Trials Experience (6.1)] as well as the Carticel worldwide experience (adverse reactions solicited through the Cartilage Repair Registry (CRR) and spontaneous reports) as of November 21, 1997 showed that the occurrence of a subsequent surgical procedure, primarily arthroscopic, following Carticel implantation is common. In the STAR study, 49% of patients underwent a subsequent surgical procedure, irrespective of relationship to Carticel (6.2). Symptoms leading to arthroscopic intervention included catching, locking, clicking or pain. Patients who develop clinical signs of tissue hypertrophy, including catching or clicking, should be evaluated and arthroscopy may be indicated for treatment or further assessment.

5.2 Risk of Transmissible Infectious Diseases

The Carticel product is intended solely for autologous use. Patients undergoing the surgical procedures associated with Carticel are not routinely tested for transmissible infectious diseases. Therefore, the cartilage biopsy and the Carticel product may carry the risk of transmitting infectious diseases to the health care provider handling these tissues. Accordingly, health care providers should employ universal precautions in handling the biopsy samples and the Carticel product.

5.3 Pre-surgical Assessment of Comorbidities

The following conditions should be assessed and treated prior to or concurrent with implantation with Carticel:

1. Unstable meniscus tears should be repaired or resected.
2. If the patient has had a total meniscectomy, absent meniscus should be reconstructed.
3. Instability of the knee may adversely affect the success of the procedure and should be corrected. The anterior and posterior cruciate ligaments should be free of laxity as well as stable and intact. It is recommended that cruciate deficiencies be corrected.
4. Abnormal weight-distribution within the joint may adversely affect the success of the procedure and should be corrected. The tibial/femoral joint should be properly aligned. When treating trochlear defects, abnormal patellar mechanics should be assessed and corrected.

5.4 Product Safety and Sterility

The safety of the Carticel product is unknown in patients with malignancy in the area of cartilage biopsy or implant. The potential exists for in vitro expansion and subsequent implantation of malignant or dysplastic cells present in biopsy tissue. In addition, implantation of normal autologous chondrocytes could theoretically stimulate growth of malignant cells in the area of the implant, although there have been no reported incidents in humans or animals.

The Carticel product is shipped following a preliminary sterility test with a 48-hour incubation to determine absence of microbial growth. Final (14 day incubation) sterility test results are not available at the time of implantation.

6. ADVERSE REACTIONS

Information on the safety of implanted autologous chondrocytes is derived from the Study of the Treatment of Articular Repair (STAR) [see Clinical Studies (14)], the Cartilage Repair Registry, the Swedish Series, and post-marketing adverse event reporting.

The most common serious adverse events (> 5% of patients) derived from the STAR study include arthrofibrosis/joint adhesion, graft overgrowth, chondromalacia or chondrosis, cartilage injury, graft complication, meniscal lesion and graft delamination. Only serious adverse events were collected in this study.

6.1 Clinical Trials Experience

The adverse reaction rates as well as the rate and type of subsequent surgical procedures from Carticel® studies of different designs cannot be directly compared amongst each other. Adverse reaction data from these studies do, however, provide a basis for identifying adverse reactions that may be related to product use and for estimating their frequency.

Study of the Treatment of Articular Repair (STAR)

In the STAR study [see Study of the Treatment of Articular Repair (STAR) (14.2.2)], patients who had experienced an inadequate response to a prior cartilage repair procedure underwent Carticel implantation to the index lesion. A total of 154 patients were implanted with Carticel; 28 patients discontinued the study early. The numbers of patients completing the 24 and 48 month follow-up visits are 136 and 115, respectively. Mean patient age was 35 years at consent. The majority of patients were Caucasian (135; 88%) and male (106; 69%).

Seventy-six (76) (49% of 154) patients underwent 113 subsequent surgical procedures (SSPs) on the treated knee, irrespective of relationship to Carticel, during the 4 year follow-up. Of the 76 patients, 52 patients had 1 SSP, 15 patients had 2 SSPs, and 9 patients had 3 or more SSPs. Sixty-one (61) (80%) of the 76 patients who had an SSP underwent a procedure within the first 24 months after implantation. The majority of patients, 83% (63 of the 76), underwent an arthroscopy or manipulation under anesthesia only. Table 1 shows the interventions during SSPs in > 2% of patients.

Table 1: Interventions during Subsequent Surgical Procedures, Regardless of Relationship, in > 2% of Patients
Intervention | % of 154 Patients
Debridement of Cartilage Lesion [Includes debridement of index lesion and other defects] | 31% (47/154)
Lysis of Adhesions | 14% (21/154)
Synovectomy / Synovial Plica Excision | 12% (19/154)
Other Debridement [Includes debridement of other joint structures in addition to cartilage (e.g., patellar fat pad)] | 10% (16/154)
Chondroplasty | 6% (10/154)
Meniscectomy | 6% (10/154)
Loose Body Removal | 5% (7/154)
Microfracture – Index Lesion | 5% (7/154)
Scar Tissue Removal | 5% (7/154)
Release of Patellar Retinaculum | 4% (6/154)
Hardware Removal | 4% (6/154)
Microfracture – New Lesion | 4% (6/154)
Osteotomy | 3% (5/154)

Lysis of adhesions was the most frequent surgical intervention performed in the first 6 months. After 6 months, cartilage debridement was the most frequently performed intervention. In the STAR study, 61% (46/76) of patients who required an SSP after Carticel did not meet failure criteria by either modified Cincinnati score or surgical criteria (e.g., graft delamination or surgical procedure violating the subchondral bone).

The most clinically significant interventions or findings involving the Carticel graft or periosteal patch are as follows: 3 Carticel grafts were completely removed and 1 was partially removed due to delamination. Partial delamination or fraying of the graft or periosteal patch was reported in 10 additional patients. Four (4) of these patients underwent reattachment/repair of the periosteal patch. Finally, a partially intact graft was found in 1 patient who was re-implanted. Detailed lists of interventions and findings that may have been associated with the graft or periosteal patch are presented in Tables 1 and 2, respectively.

Table 2 shows the serious adverse events (SAEs) that occurred in ≥ 5% of patients, regardless of relationship to study treatment.

Table 2: Most Frequent Serious Adverse Events (in ≥ 5% of Patients), Regardless of Relationship, in the STAR Study
Serious Adverse Events | % of 154 Patients
Arthrofibrosis/Joint Adhesions | 16% (25/154)
Graft Overgrowth | 15% (23/154)
Chondromalacia or Chondrosis | 12% (18/154)
Cartilage Injury [Encompasses cartilage injuries throughout the joint e.g., onset of new defects and tibial plateau fibrillation] | 11% (17/154)
Graft Complication [Includes periosteal patch complications, graft fraying or fibrillation] | 10% (15/154)
Meniscal Lesion | 8% (12/154)
Graft Delamination | 6% (9/154)
Osteoarthritis | 5% (7/154)

Registry Based Study (RBS)

Data from a cohort of 97 Carticel® treated patients, who were retrospectively evaluated in the Registry Based Study [see Registry-Based Study (RBS) (14.2.1)], showed that 39% (38/97) of patients had a SSP within 3 years of which 63% (24/38) were assessed as related to Carticel. Shaving or trimming (debridement) of overgrown tissue (hypertrophic) commonly relieved patients' symptoms. In the RBS, 67% (16/24) of patients who required arthroscopy after Carticel had a good clinical benefit in terms of improved function and relief of symptoms. Table 3 shows the findings at surgery for the 38 patients who underwent a surgical procedure after Carticel.

Table 3: Most Frequent Findings (in ≥ 5% of Patients) at Subsequent Surgical Procedures in the Registry Based Study
Symptoms or Surgical Findings (MedDRA preferred term) | % of 97 Patients
Graft Overgrowth | 10% (10/97)
Partial Graft Delamination | 8% (8/97)
Chondromalacia | 8% (8/97)
Arthrofibrosis/Joint Adhesions | 8% (8/97)
Arthralgia | 7% (7/97)
Synovitis | 6% (6/97)
Meniscal Lesion | 5% (5/97)
Loose Body | 5% (5/97)

Swedish Series

Of 153 patients treated with autologous cultured chondrocyte implantation in the Swedish Series [see Clinical Studies (14)], 22% (34/153) of patients experienced the adverse reactions presented in Table 4 below.

Table 4: Initial ACI Experience Swedish Series Serious Adverse Reactions (Occurring at a frequency of 1% or more)
Serious Adverse Reactions | % of 153 Patients
Tissue Hypertrophy | See below
Intra-articular Adhesions | 8%
Superficial Wound Infection | 3%
Hypertrophic Synovitis | 3%
Post-operative Hematoma | 2%
Adhesions of the Bursa Suprapatellaris | 2%
Hypertrophic Synovium | 1%

About 1% of patients developed severe adhesions resulting in "frozen knee" and requiring lysis. Adverse reactions noted at a level of less than 1% included keloid-like scar, pannus formation, significant swelling of the joint, pain with post-operative fever, and hematoma following arthroscopy.

In this series, arthroscopy was scheduled to be undertaken at 18 months of follow-up, regardless of patient symptoms. Of the patients who had arthroscopy, 43% (37/86) had hypertrophic tissue.

Forty of the 85 patients had femoral condyle defects. Of these, 25% (10/40) of patients had some hypertrophic tissue noted at follow-up arthroscopy. Some patients had clinical symptoms that included painful crepitations or catching, and these symptoms generally resolved after arthroscopic resection of the hypertrophic tissue. Ten percent (10%) of patients with hypertrophy required additional treatment after hypertrophic tissue recurred following initial resection. Not all patients with tissue hypertrophy noted at arthroscopy were symptomatic.

6.2 Postmarketing Experience

The following adverse reactions have been identified during post-approval use of Carticel®. Most of these reactions are reported voluntarily, and it is not always possible to reliably estimate their frequency or establish a causal relationship to drug exposure. Furthermore, the reported frequency of spontaneous reports underestimates the true frequency of adverse reactions. As of July 31, 2006, approximately 12,500 patients have been implanted with Carticel and 559 patients have reported serious adverse reactions after treatment. The most frequently identified operative findings in these patients, in descending order of frequency, were graft overgrowth, graft delamination (partial or complete), arthrofibrosis, joint adhesions, meniscus lesion or tear, graft complications, chondromalacia, loose body in knee joint, and joint malalignment.

8. USE IN SPECIFIC POPULATIONS

8.4 Pediatric Use

Safety and effectiveness in pediatric patients have not been established.

8.5 Geriatric Use

Clinical studies of Carticel did not include sufficient numbers of subjects aged 65 and over to determine whether they respond differently from younger subjects.

11. DESCRIPTION

Autologous cultured chondrocytes, the Carticel product, are derived from in vitro expansion of chondrocytes harvested from the patient's normal, femoral articular cartilage. Biopsies from a lesser-weight bearing area are the source of chondrocytes, which are isolated, expanded through cell culture, and implanted into articular cartilage defects beneath an autologous periosteal flap. Prior to final packaging, cell viability is assessed to be at least 80%.

Each single use container of autologous cultured chondrocytes has approximately 12 million cells aseptically processed and suspended in 0.4 mL of sterile, buffered Dulbecco's Modified Eagles Medium (DMEM). Both the biopsy transport media and the cell culture media contain gentamicin. Residual quantities of gentamicin up to 5 µg/mL may be present in the Carticel product.

12. CLINICAL PHARMACOLOGY

Hyaline cartilage forms the articular surface of the femoral condyle. Studies have shown that implantation of autologous chondrocytes into the articular defect can result in the development of hyaline-like cartilage [see Clinical Studies (14)].^1,2,3,4,5 Normal hyaline cartilage consists of chondrocytes (≤ 5% total volume) and extracellular matrix (≥ 95% total volume). The matrix contains a variety of macromolecules, including type II collagen and proteoglycan. The structure of the matrix allows the hyaline cartilage to absorb shock and withstand shearing and compression forces. Normal hyaline cartilage also has an extremely low coefficient of friction at the articular surface. Damage to articular cartilage from acute or repetitive trauma often results in pain and disability. However, because hyaline cartilage is avascular, spontaneous healing of large defects is not believed to occur in humans.

A variety of surgical procedures have been used in attempts to promote repair of articular cartilage, and a few studies have evaluated the histology resulting from these interventions. Generally, procedures such as marrow stimulation techniques (MST) have been shown to produce fibrocartilage or hybrid mixtures of fibrocartilage and hyaline cartilage. Published data show that autologous chondrocyte implantation (ACI) is more likely than MST to result in hyaline-like cartilage at the repair site. ^1,2,4,5 However, because of differences in study design, lesion size and concomitant patient conditions, these data are not sufficient to draw conclusions concerning the long-term correlation of histology and clinical outcomes.

13. NONCLINICAL TOXICOLOGY

13.1 Carcinogenesis, Mutagenesis, Impairment of Fertility

No carcinogenicity or mutagenicity data are available for Carticel in animals or in humans. No studies on the effects of Carticel on fertility have been conducted.

13.2 Animal Pharmacology and/or Toxicology

Pre-Approval Studies

Bioactivity of autologous chondrocytes implanted under a periosteal patch was reported in the BLA for three rabbit studies^6,7,8 of up to 52 weeks duration post-implant and one dog study^9 of up to 18 months duration post-implant.

Rabbit Studies

- Histologic evaluations were performed at 8, 12 and 52 weeks. Improved healing of experimental defects implanted with autologous chondrocytes was observed compared to periosteal flap alone at 8, 12 and 52 weeks.

Dog Study

- Histologic evaluations were performed at 6 and 12 weeks and 12 and 18 months. Autologous chondrocytes showed improved healing compared to both empty defects and to defects covered with periosteum alone at 6 and 12 weeks. However, by the 12 and 18 month evaluations, the repair tissue had deteriorated so that no advantage of ACI over periosteum alone controls was demonstrated.

Beyond histologic variability of the defect site, no adverse tissue reaction was identified in any animals in these studies.

Post-Approval Studies

Five additional large animal, post-approval studies were performed.

Goat Studies

- Three of four goat studies were 16 weeks in duration. In the fourth study, the goats were sacrificed immediately after periosteal membrane placement. Despite difficulty in post-operative management of goats and resulting subchondral plate collapse in some animals in the 16-week studies, results from all four studies suggested that chondrocytes may contribute to histological repair of focal cartilage lesions. In the only bilateral joint study, serious subchondral collapse and uniformly poor repair resulted in inconclusive data. No safety issues were identified in any of these studies.

Horse Study

- The 8-week study included two experimental arms in order to model repair of cartilage lesions with or without subchondral penetration. Both models exhibited destruction/dislodgement of the periosteal flap; however, results suggested that chondrocytes may contribute to histologic repair in cartilage defects with subchondral penetration.

While the defects in all animal models exhibited highly variable repair tissue quality (resulting in only moderate histologic scores) the best repairs with implanted chondrocytes produced hyaline-like cartilage characterized by matrix predominating in type II collagen and saffranin-O or toluidine blue staining proteoglycan. Chondrocyte labeling in one of the rabbit studies^8 and in an independent study in goats by Dell'Accio et al^10 demonstrated that the hyaline-like matrix in these defects was the product of the implanted autologous chondrocytes.

14. CLINICAL STUDIES

14.1 Pre-Approval Studies

Clinical information regarding the use of autologous cultured chondrocytes was obtained from 2 open-label, observational studies consisting of a series of patients treated in Sweden and the Cartilage Repair Registry. Patients in the Swedish series received an autologous cultured chondrocyte product similar to Carticel®.

14.1.1 Swedish Series

The series consists of 153 patients who received autologous chondrocyte implantation for various defects of the knee. Patients presented with cartilage defects of the femoral condyle, patella, tibia, a combination of these, or osteochondritis dissecans, with or without comorbidity such as anterior cruciate ligament insufficiency requiring reconstruction.

Following autologous chondrocyte implantation, patients were followed for various durations. Clinical follow-up ranged from 1 week to 94 months; 86 patients had at least 18 months of follow-up. Most patients had arthroscopic evaluation; a subset had biopsy and histological evaluations. All patients were retrospectively classified as having one of three clinical outcomes: resumed all activities, some improvement, or no improvement. Clinical outcomes were also reported for patient subgroups including: 1) 40 patients with femoral condyle lesions, 2) 12 patients with osteochondritis dissecans lesions and 3) 22 patients who failed a prior debridement.

1) Clinical Outcome - Patients with Femoral Condyle Lesions

A total of 78 of 153 patients had femoral condyle lesions with or without co-morbidity. Patients had one or more defects ranging in size from < 1-20 cm^2. Of the patients with femoral condyle lesions, 40 were evaluable after at least 18 months (median = 25; range = 18 to 94 months). Clinical outcomes for the 40 patients are summarized in Table 5.

Table 5: Patient Response to Treatment
Defect | Resumed All Activities | Some Improvement | No Improvement | Total Patients
Femoral Condyle | 7 (29%) | 8 (33%) | 9 (38%) | 24
Femoral Condyle plus other Non-Cartilage Repair | 4 (25%) | 9 (56%) | 3 (19%) | 16
Total | 11 (28%) | 17 (42%) | 12 (30%) | 40

2) Clinical Outcome – Patients with Osteochondritis Dissecans Lesions

Of the 12 patients who received autologous cultured chondrocytes for treatment of an osteochondritis lesion, 6 of the 12 had "resumed all activities", 4 had "some improvement" and 2 had "no improvement" after the 18-month (median = 25; range = 18-94 months) follow-up period.

3) Clinical Outcome – Failed Earlier Procedures

Debridement of the cartilage defect is often performed along with administration of autologous cultured chondrocytes. To help differentiate the effects of the autologous cultured chondrocyte implantation procedure from those of debridement alone, an analysis was performed on 22 patients who had failed prior debridement and had a follow-up period after autologous cultured chondrocyte implantation which was at least as long as the time period to failure of their initial debridement. At the end of follow-up, 5 of the 22 patients had a functional outcome rating of "resumed all activities", 8 of the 22 patients had a rating of "some improvement" and 9 of the 22 patients had a rating of "no improvement." Thus, 13 of the 22 patients (59%) who had failed an earlier debridement had outcomes that were more favorable and durable following autologous cultured chondrocyte implantation than their previous debridement without cells.

Histological Outcome

Twenty-two (22) patients in the Swedish series had histological evaluation of biopsies from the implant site one or more years after their autologous chondrocyte implantation. Fifteen (15) of those patients had defects of the femoral condyle and 7 had defects of the patella. Six (6) of the 15 femoral condyle biopsies showed hyaline-like cartilage, 5 had a mixture of hyaline and fibrocartilage, and 4 had only fibrocartilage. Of the 6 biopsies with hyaline-like cartilage, 2 had minimal to no surface irregularities and 4 had some surface irregularities (e.g., fissures, fibrillations, etc.).

Arthroscopic Outcome

As an objective outcome evaluation, 86 of the 153 patients had a follow-up arthroscopy for investigational purposes at 18 months or more post-implantation. In some cases, the quality of repair observed at arthroscopy was considered to be supportive of the clinical or functional outcomes. A substantial number of patients were noted at arthroscopy to have tissue hypertrophy [see Adverse Reactions (6)].

14.1.2 Cartilage Repair Registry

The Cartilage Repair Registry (CRR) was established upon the introduction of Carticel® into orthopedic practice in March of 1995. The CRR was designed to prospectively collect the clinical outcomes of Carticel and other cartilage repair treatments for chondral lesions in the knee. Clinical data were collected at baseline arthroscopy, implantation, intervals of 6 and 12 months, and annually thereafter; adverse reaction data were collected on an ongoing basis through CRR adverse reaction collection and spontaneous reporting. Inclusion in the CRR was based on a qualifying event that was defined as a knee arthroscopy in which a chondral lesion was identified and a cartilage biopsy was harvested. Participation in the CRR was voluntary, and not all patients biopsied or implanted were included. As of November 21, 1997, 891 patients had been implanted worldwide, and 644 of these patients were included in the CRR. Functional outcomes were based on responses to a modified version of the Cincinnati Knee Rating System.

Data from a subset of 191 US patients in the CRR as of December 31, 1996 who had undergone repair of lesions on the femoral condyle (medial, lateral or trochlea) were assessed to support licensure. Patients were between the ages of 15-57, 66% (126/191) were male, and 34% (64/191) were female and one patient's gender was not reported. Of these 191 patients, 38 had at least 12 months of follow-up. At study baseline, these 38 patients' mean rating of overall condition was 3.2, which is defined as fair to poor: limitations that affect activities of daily living-no sports possible. At 12 month follow-up, these patients reported an overall condition score of 6.4 defined as good: some limitation with sports but can participate if patient compensates. Although these patients were rated according to outcome measurements different from those used in the Swedish series, the results were consistent with the Swedish experience.

14.2 Post-Approval Studies

Two post-approval studies were conducted and completed as a condition of approval for Carticel®: the Registry Based Study (RBS) and the Study of the Treatment of Articular Repair (STAR).

14.2.1 Registry-Based Study (RBS)

The RBS was a retrospective analysis of data collected for a cohort of 97 US patients treated between March of 1995 and March of 1997. Of the 97 patients enrolled, 95% completed 1-year follow-up, 80% completed 2-year follow-up and 74% completed 3-year follow-up. Of these 97 patients, 44 were part of the subset of 191 US patients in the CRR described above. A limitation of this study is the lack of a control group. Patients included in this study had a prior non-Carticel cartilage repair procedure (e.g., debridement or marrow stimulation procedure) performed at the time of the index arthroscopy, subsequently failed this procedure and went on to receive Carticel. In the 5 years prior to the index arthroscopy for the study, this patient population had received prior knee surgeries to include: 47% (46/97) of patients had at least one debridement/lavage of a cartilage defect, 25% (24/97) of patients had a bone marrow stimulation procedure, 31% (30/97) had at least one diagnostic arthroscopy, 30% (29/97) had at least one meniscus repair/meniscectomy and 10% (10/97) of patients had a ligament repair/reconstruction performed on the treated knee.

Using a modified Cincinnati Knee Rating System at study baseline, this patient population had a mean overall condition score of 3.1 defined as fair to poor: limitations that affect activities of daily living-no sports possible. Patients included were between the ages of 16-56, 69% (67/97) were male and 31% (30/97) were female. For the type of defect, 62% (60/97) of the defects were acute while 37% (36/97) were chronic. Of the treated defects, 75% (73/97) were treated on the medial femoral condyle (MFC), 26% (25/97) on the lateral femoral condyle (LFC) and 19% (18/97) on the trochlea. Adverse reactions collected during this study are provided in Adverse Reactions (6).

14.2.2 Study of the Treatment of Articular Repair (STAR)

The STAR study was an open-label within patient comparison of a prior non-Carticel (index) procedure to implantation of Carticel for articular cartilage defects of the distal femur. All patients had experienced an inadequate response to a prior non-Carticel surgical treatment, defined as both: a) patient and surgeon agreement that the patient's symptoms/function required surgical re-treatment of the defect and b) the patient's rating of the overall condition of the knee was a score ≤ 5 using the Modified Cincinnati Knee Rating System. In this patient population, the median time to meet the failure criteria was 3.4 months for the prior non-Carticel procedure and 90% of patients failed within 10.3 months. Patients who met these criteria were treated with Carticel and assessed every 6 months for up to 4 years.

Treatment failure for Carticel was defined as any of the following: a) the patient underwent surgical retreatment that violated the subchondral bone or reimplantation with Carticel for the same index defect, b) complete delamination or removal of the graft, or c) the patient's rating of the overall condition of the knee using the Modified Cincinnati Knee Rating System failed to improve from the baseline knee score over 3 consecutive 6-month intervals.

A total of 154 patients were treated with Carticel. At the index surgery required for study entry, patients had one or more of the following interventions: 120 patients (78%) had debridement, 44 patients (29%) had microfracture, 18 (12%) had subchondral drilling, 10 (6%) had abrasion arthroplasty, and 7 (5%) had an osteochondral autograft. The mean lesion size was 4.6 (± 3.2, SD) cm^2. Fifty patients (32%) had multiple lesions in the reference knee and 29 patients had Carticel implanted in more than one lesion. Lesions that were implanted were located on the medial femoral condyle in 109 patients, lateral femoral condyle in 32 patients and trochlea in 46 patients. Forty patients (26%) had lesions which involved osteochondritis dissecans (OCD).

Of the 154 patients treated with Carticel, 28 patients discontinued the study early. The numbers of patients completing the 24 and 48 month follow-up visits are 136 and 115, respectively. The majority of Carticel patients (N= 117) did not meet failure criteria during the study. By the end of the study, a total of 37 patients met the treatment failure criteria. Results for the 40 patients with OCD lesions were comparable to the total study population as 34 (85%) did not meet the failure criteria for the study and 6 (15%) failed treatment with Carticel. Table 6 illustrates, during each year of follow-up, the number of patients who failed Carticel by the surgical criteria along with the number of patients who failed by the Overall Modified Cincinnati scale criteria.

Table 6: Category and Timing of Treatment Failure for Patients who Met Treatment Failure Criteria (N=37)
 | 1 Year | 2 Years | 3 Years | 4 Years | Total
Patients who Failed During the Interval | 14 | 11 | 11 | 1 | 37
Surgery criteria | 0 | 5 | 5 | 1 | 11
Overall Modified Cincinnati Scale criteria | 14 | 6 | 6 | 0 | 26

The Overall Modified Cincinnati mean baseline score for the patient population as a whole was 3.26, poor: significant limitations that affect activities of daily living, to fair: moderate limitations that affect activities of daily living, no sports possible. At 48 months, the mean score was 6.39, good: some limitations with sports but can participate/compensate. The improvement was statistically significant. Table 7 shows the improvement in the Overall Modified Cincinnati score over time.

Table 7: Mean Overall Modified Cincinnati Score at Baseline and Follow-up Visits
Visit | Baseline N=154 | Month 12 N=146 | Month 24 N=131 | Month 36 N=104 | Month 48 N=101
Overall Modified Cincinnati Score [Scores are for patients who returned for follow-up. Patients who failed by score criteria are included and patients who failed by surgical criteria are excluded from the scores for timepoints after the failure criteria were met.] Mean (SD) | 3.26 (1.02) | 5.58 (1.99) | 5.92 (2.08) | 5.87 (2.19) | 6.39 (2.31)

In addition to the change over time in activity level as measured with the Overall Modified Cincinnati Scale, there were similar and consistent changes in knee symptoms and function as measured with the Knee Injury and Osteoarthritis Outcome Score (KOOS), a measure of knee-specific symptoms and function consisting of the following five subscales: pain, symptoms, sports and recreation, knee-related quality of life, and activities of daily living. At 12 months post-Carticel® implant, the mean improvement from baseline for the patient population as a whole in each subscale was as follows: pain 19 (N = 146), symptoms 15 (N = 147), sports and recreation 17 (N = 129), knee-related quality of life 18 (N = 147), and activities of daily living 18 (N = 145). At 48 months post-Carticel implant, the mean improvement from baseline was as follows: pain 24 (N = 100), symptoms 19 (N = 101), sports and recreation 31 (N = 86), knee-related quality of life 32 (N = 101), and activities of daily living 23 (N = 99).

Adverse reactions collected during this study are provided in Adverse Reactions (6).

15. REFERENCES

1. Knutsen G, Engebretsen L, Ludvigsen T, et al. Autologous chondrocyte implantation compared with microfracture in the knee. J Bone Joint Surg, 2004; 86A:455-464.
2. Bentley G, Biant LC, Carrington RWJ, et al. A prospective, randomized comparison of autologous chondrocyte implantation versus mosaicplasty for osteochondral defects in the knee. J Bone Joint Surg Br. 2003;85-B:223-230.
3. Brittberg M, Lindahl A, Nilsson A, et al. Treatment of deep cartilage defects in the knee with autologous chondrocyte transplantation. N Engl J Med. 1994;331:889-895.
4. Peterson L, Minas T, Brittberg M, et al. Two- to 9-year outcome after autologous chondrocyte transplantation of the knee. Clin Orthop. 2000;1(374):212-234.
5. Peterson L, Brittberg M, Kiviranta I, et al. Autologous chondrocyte transplantation. Biomechanics and long-term durability. Am J Sports Med. 2002;30:2-12.
6. Peterson L, Menche D, Grande D, et al. Chondrocyte transplantation-an experimental model in the rabbit. Transactions from the 30th Annual Orthopedic Research Society, Atlanta, February 7-9, 1984. Palatine, III.:Orthopedic Research Society, 1984:218. Abstract.
7. Grande DA, Pitman MI, Peterson L, et al. The repair of experimentally produced defects in rabbit articular cartilage by autologous chondrocyte transplantation. J Orthop Res. 1989;7(2):208-18.
8. Brittberg M, Nilsson A, Lindahl A, et al. Rabbit articular cartilage defects treated with autologous cultured chondrocytes. Clin Orthop Relat Res. 1996 May;(326):270-83.
9. Breinan H, Minas T, Barone L, et al. Histological evaluation of the course of healing of canine articular cartilage defects treated with cultured autologous chondrocytes. Tiss Engin 1998; 4(1):101-14.
10. Dell'Accio F, Vanlauwe J, Bellemans, et al. Expanded phenotypically stable chondrocytes persist in the repair tissue and contribute to cartilage matrix formation and structural integration in a goat model of autologous chondrocyte implantation. Journal of Orthopaedic Research 21 2003; 21: 123–131.

16. HOW SUPPLIED/STORAGE AND HANDLING

16.1 How Supplied

The Carticel product, NDC 69866-1025-1, consists of viable, autologous cells packaged and labeled for implantation within specified time limits. Each vial contains approximately 12 million autologous cells for a single implantation procedure.

The shipping vials containing chondrocytes are accompanied by a technical data sheet with detailed specifications for the processed cells. The vial(s) of cells is placed within secondary packaging capable of maintaining the appropriate storage temperature and cell viability for up to 72 hours.

16.2 Storage and Handling

The Carticel® transport box should be held at room temperature and remain closed until the time of implantation to ensure proper storage conditions for the cells.

Do Not Refrigerate, Freeze, or Incubate the Carticel Shipping Container or its Contents.

Do Not Sterilize.

If the Vial is Damaged or Sterility has been Compromised, Do Not Use.

17. PATIENT COUNSELING INFORMATION

Patients receiving autologous cultured chondrocytes for treatment of an articular cartilage defect should receive the following information and instructions.

- Physical activity should be resumed according to the rehabilitation plan recommended by the physician. Generally, protected weight bearing is recommended for the first 6 to 8 weeks following implantation. The patient should receive specific instructions on crutch use, ambulation and weight bearing advancement on the treated limb.
- If pain starts to develop as the next level of activity is increased, decrease activity to the former level until the pain resolves.
- If exercise causes pain and/or swelling, reduce the amount of physical activity.
- Swelling should be controlled using ice packs.
- Patient adherence to the prescribed rehabilitation program is important and activity at variance from the rehabilitation program may compromise clinical benefit from Carticel.
- At anytime during the rehabilitation process or after, if sharp pain with locking or swelling is experienced, contact the physician for medical advice.

Vericel Corporation
64 Sidney Street
Cambridge, MA 02139-4136 USA
Telephone: 800-453-6948 or 617-588-5566
Fax: 844-333-2847

Carticel® is a Registered Trademark of Vericel Corporation.

65001
Revision M
11/2015

PRINCIPAL DISPLAY PANEL - 0.4 mL Vial Label

Autologous
Cultured
Chondrocytes

Lot #: {LOT # - Ext}
Patient ID# : {PtID}
Expiry: {HH:MM} {Zn}
{DD MMM YY}
Vericel Corporation
Cambridge, MA 02139 Lic: 2010
Rx only
Label #: 63014.K 11/2015

PRINCIPAL DISPLAY PANEL - 0.4 mL Vial Shipping Label

Autologous Cultured Chondrocytes
Carticel®
FOR AUTOLOGOUS USE ONLY
NOT EVALUATED FOR INFECTIOUS SUBSTANCES
Vericel Corporation Patient ID #: {Patient ID}
{Patient Initials}
{Hospital Name}
Lot #:{LOT # - Ext}
Expiry: {HH:MM} {Zn} {DD MMM YY}
Store at room temperature. DO NOT FREEZE
({#})vial(s) approximately 12 million cells per vial in 0.4 mL DMEM
for implantation. No US Standard of Potency. NO PRESERVATIVES
Cells Expanded in Medium Containing 44 mcg/mL Gentamicin
See Insert for Complete Instructions and Dosing
Rx Only
Vericel Corporation
Cambridge, MA 02139 USA
Carticel® is a registered trademark of Vericel Corporation
Label #: 64014.J - 11/2015
License #: 2010

Principal Display Panel - 0.4 mL Vial Carton Label

Autologous Cultured Chondrocytes
Carticel®
FOR AUTOLOGOUS USE ONLY
NOT EVALUATED FOR INFECTIOUS SUBSTANCES
Vericel Corporation Patient ID #: {Patient ID}
{First Mid Last}
{Hospital Name}
Lot #: {LOT #} - {Ext}
Expiry: {HH:MM}{Zn} {DDMMMYY}
Store at room temperature. DO NOT FREEZE
STORE CONTAINER IN SHIPPING BOX AS RECEIVED.
{#}vial(s) approximately 12 million cells per vial in 0.4 mL DMEM
for implantation. No US Standard of Potency. NO PRESERVATIVES
Cells Expanded in Medium Containing 44 mcg/mL Gentamicin
See Insert for Complete Instructions and Dosing
Rx Only
Vericel Corporation
Cambridge, MA 02139 USA
Carticel® is a registered trademark of Vericel Corporation
Label #: 64090.D 11/2015
License #: 2010